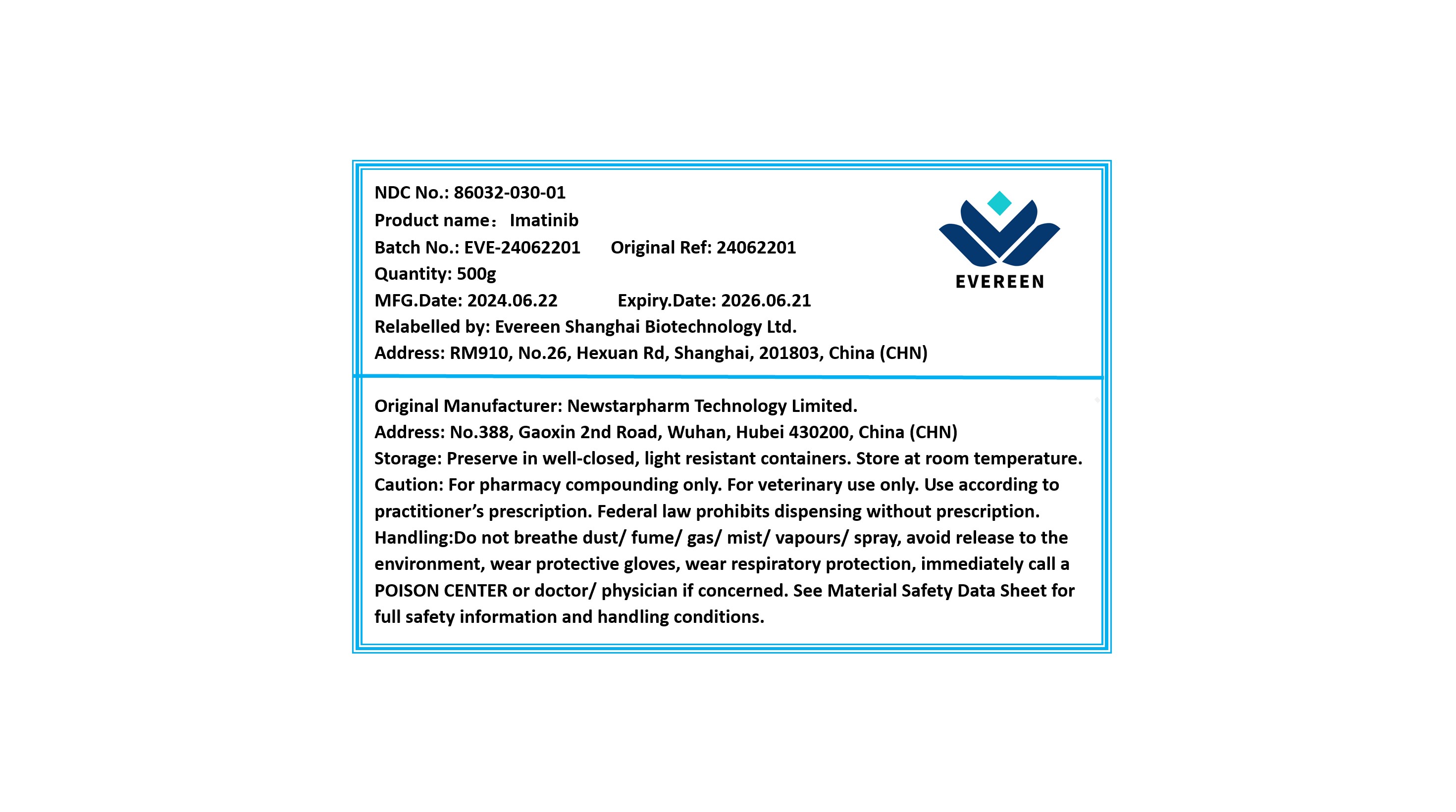 DRUG LABEL: Imatinib
NDC: 86032-030 | Form: POWDER
Manufacturer: Evereen Shanghai Biotechnology Ltd.
Category: other | Type: BULK INGREDIENT - ANIMAL DRUG
Date: 20240904

ACTIVE INGREDIENTS: IMATINIB 1 g/1 g

Imatinib